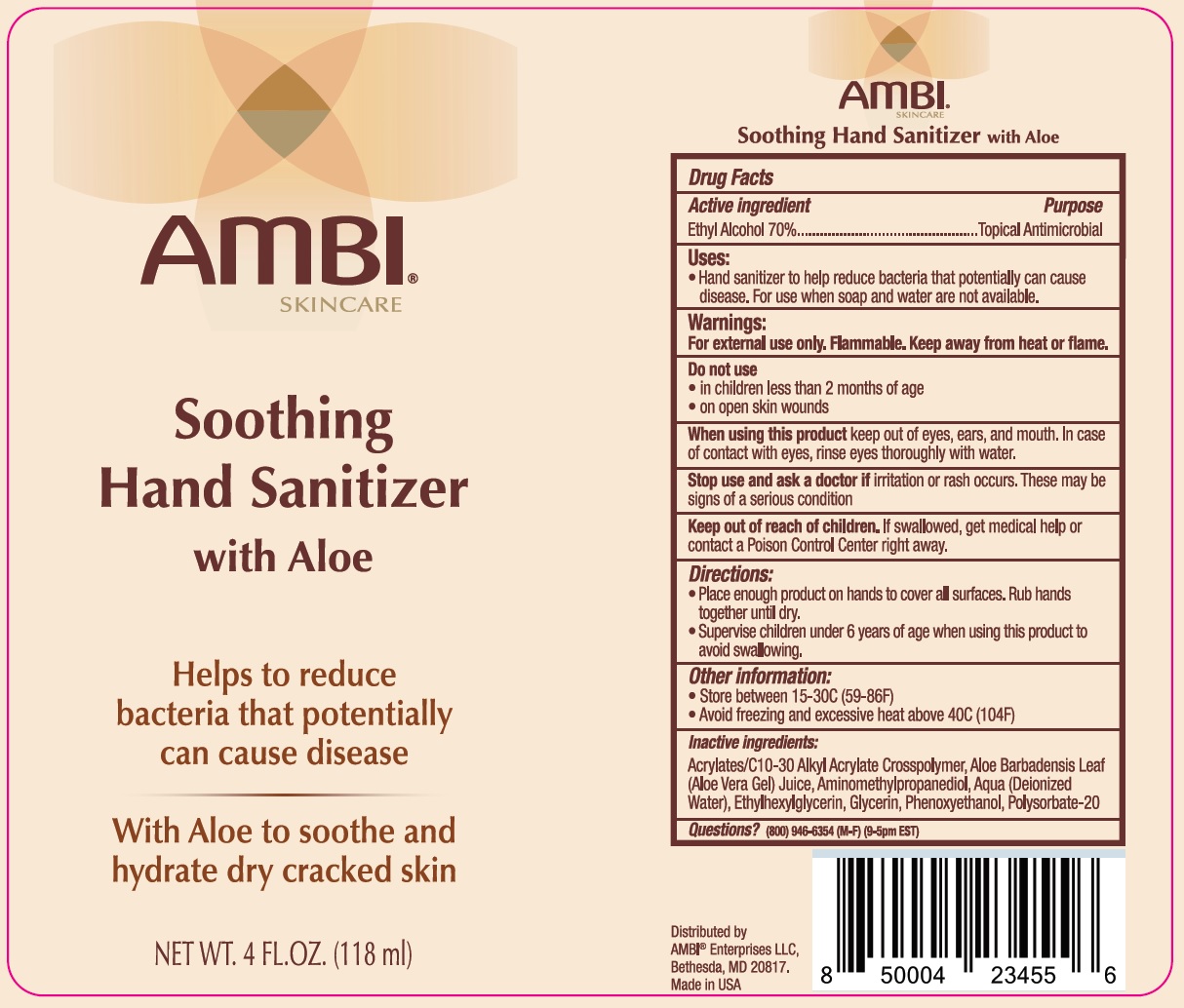 DRUG LABEL: AMBI Soothing Hand sanitizer
NDC: 73453-143 | Form: GEL
Manufacturer: AMBI Enterprises, llc
Category: otc | Type: HUMAN OTC DRUG LABEL
Date: 20231105

ACTIVE INGREDIENTS: ALCOHOL 0.7 mL/1 mL
INACTIVE INGREDIENTS: CARBOMER INTERPOLYMER TYPE A (ALLYL SUCROSE CROSSLINKED); ALOE VERA LEAF; AMINOMETHYL PROPANEDIOL; WATER; ETHYLHEXYLGLYCERIN; GLYCERIN; PHENOXYETHANOL; POLYSORBATE 20

AMBI Soothing Hand sanitizer

Active ingredient

Ethyl Alcohol 70%

Purpose

Topical Antimicrobial

Uses:

- Hand sanitizer to help reduce bacteria that potentially can cause disease. For use when soap and water are not available.

Warnings:

For external use only. Flammable. Keep away from heat or flame.

Do not use

- in children less than 2 months of age
- on open skin wounds

When using this product

keep out of eyes, ears, and mouth. In case of contact with eyes, rinse eyes thoroughly with water.

Stop use and ask a doctor if

irritation or rash occurs. These may be signs of a serious condition

Keep out of reach of children.

If swallowed, get medical help or contact a Poison Control Center right away.

Directions:

- Place enough product on hands to cover all surfaces. Rub hands together until dry.
- Supervise children under 6 years of age when using this product to avoid swallowing.

Other information:

- Store between 15-30C (59-86F)
- Avoid freezing and excessive heat above 40C (104F)

Inactive ingredients:

Acrylates/C10-30 Alkyl Acrylate Crosspolymer, Aloe Barbadensis Leaf (Aloe Vera Gel) Juice, Aminomethylpropanediol, Aqua (Deionized Water), Ethylhexylglycerin, Glycerin, Phenoxyethanol, Polysorbate-20

Questions?

(800) 946-6354 (M-F) (9-5pm EST)